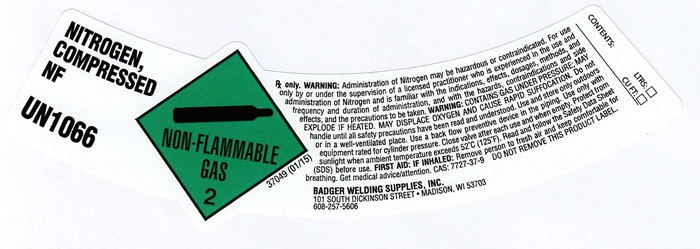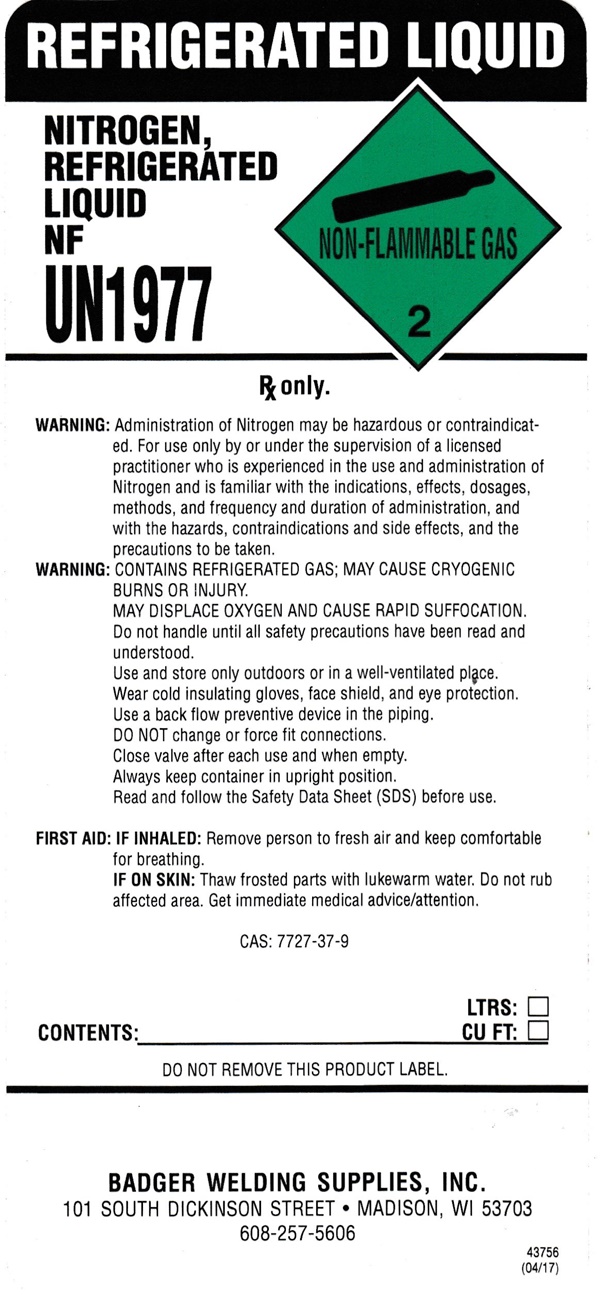 DRUG LABEL: NITROGEN
NDC: 12121-006 | Form: GAS
Manufacturer: Badger Welding Supplies, Inc.
Category: prescription | Type: HUMAN PRESCRIPTION DRUG LABEL
Date: 20241012

ACTIVE INGREDIENTS: NITROGEN 99 L/100 L

NITROGEN - 006

NITROGEN NF COMPRESSED product label

NITROGEN COMPRESSED NF

UN 1966

NON-FLAMMABLE GAS 2

37049 (1/15)

Rx only. WARNING:Administration of Nitrogen may be hazardous or contraindicated. For use only by or under the supervision of a licensed practitioner who is experienced in the use and administration of Nitrogen and is familiar with the indications, effects, dosages, methods, and frequency and duration of administration, and with the hazards, contraindications and side effects, and the precautions to be taken. WARNING: CONTAINS GAS UNDER PRESSURE; MAY EXPLODE IF HEATED. MAY DISPLACE OXYGEN AND CAUSE SUFFOCATION. Do not handle until all safety precautions have been read and understood. Use and store only outdoors or in a well-ventilated place. Use a back flow preventive device in the piping. Use only withequipment rated for cylinder pressure. Close valve after each use and when empty. Protect from sunlight when ambient temperature exceeds 52°C (125°F). Read and follow the Safety Data Sheet (SDS) before use. FIRST AID: IF INHALED: Remove person to fresh air and keep comfortable for breathing. get medical advice/attention. CAS: 7727-37-9 DO NOT REMOVE THIS PRODUCT LABEL

BADGER WELDING SUPPLIES, INC.

101 SOUTH DICKINSON STREET • MADISON, WI 53703

608-257-5606

CONTENTS:

LTRS:

CU FT:

REFIGERATED LIQUID NITROGEN REFRIGERATED LIQUID NF product label

REFIGERATED LIQUID
NITROGEN REFRIGERATED LIQUID NF
UN1977

NON-FLAMMABLE GAS 2

Rx only.

WARNING: Administration of Nitrogen may be hazardous or contraindicated. For use only by or under the supervision of a licensed practitioner who is experienced in the use and administration of Nitrogen and is familiar with the indications, effects, dosages, methods, and frequency and duration of administration, and with the hazards, contraindications and side effects and the precautions to be taken.

WARNING: CONTAINS REFIGERATED GAS: MAY CAUSE CRYOGENIC BURNS OR INJURY.

MAY DISPLACE OXYGEN AND CAUSE RAPID SUFFOCATION

Do not handle until all safety precautions have been read and understood.

Use and store only outdoors or in a well-ventilated place.

Wear cold insulating gloves, face shield, and eye protection.

Use a back flow preventive device in the piping.

DO NOT change or force fit connections.

Close valve after each use and when empty.

Always keep container in upright position.

Read and follow the Safety Data Sheet (SDS) before use.

FIRST AID: IF INHALED: Remove person to fresh air and keep comfortable for breathing.

IF ON SKIN: Thaw frosted parts with lukewarm water. Do not rub affected area. Get immediate medical advice/attention

CAS: 7727-37-9

CONTENTS: ____________________________________________LTRS: _______________________________CU FT:

DO NOT REMOVE THIS PRODUCT LABEL

BADGER WELDING SUPPLIES, INC.
101 SOUTH DICKINSON STREET • MADISON, WI 53703

608-257-5606

43756 (04/17)